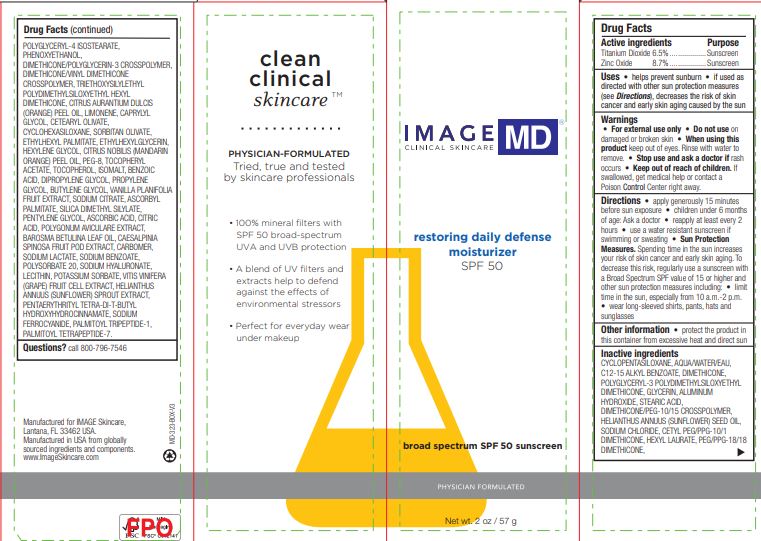 DRUG LABEL: MD Restoring daily Defense Moisturizer SPF 50
NDC: 62742-4220 | Form: CREAM
Manufacturer: Allure Labs Inc
Category: otc | Type: HUMAN OTC DRUG LABEL
Date: 20241209

ACTIVE INGREDIENTS: ZINC OXIDE 8.7 g/100 g; TITANIUM DIOXIDE 6.5 g/100 g
INACTIVE INGREDIENTS: ALKYL (C12-15) BENZOATE; DIMETHICONE; POLYGLYCERYL-3 POLYDIMETHYLSILOXYETHYL DIMETHICONE (4000 MPA.S); SUNFLOWER OIL; HEXYLENE GLYCOL; MANDARIN OIL; SORBITAN OLIVATE; AGATHOSMA BETULINA LEAF OIL; STEARIC ACID; SODIUM CHLORIDE; HEXYL LAURATE; PEG/PPG-18/18 DIMETHICONE; ETHYLHEXYL PALMITATE; .ALPHA.-TOCOPHEROL ACETATE; TOCOPHEROL; BENZOIC ACID; DIPROPYLENE GLYCOL; PROPYLENE GLYCOL; BUTYLENE GLYCOL; VANILLA; SODIUM CITRATE; ASCORBYL PALMITATE; PENTYLENE GLYCOL; CITRIC ACID MONOHYDRATE; POLYGONUM AVICULARE TOP; CAESALPINIA SPINOSA FRUIT POD; SODIUM LACTATE; SODIUM FERROCYANIDE; POLYSORBATE 20; VITIS VINIFERA ANTHOCYANINS; PENTAERYTHRITOL TETRAKIS(3-(3,5-DI-TERT-BUTYL-4-HYDROXYPHENYL)PROPIONATE); PALMITOYL TRIPEPTIDE-1; PALMITOYL TETRAPEPTIDE-7; POLYGLYCERYL-4 ISOSTEARATE; DIMETHICONE/PEG-10/15 CROSSPOLYMER; ALUMINUM HYDROXIDE; HELIANTHUS ANNUUS SPROUT; POLYETHYLENE GLYCOL 400; DIMETHICONE/POLYGLYCERIN-3 CROSSPOLYMER; ETHYLHEXYLGLYCERIN; TRIETHOXYSILYLETHYL POLYDIMETHYLSILOXYETHYL HEXYL DIMETHICONE; DIMETHICONE/VINYL DIMETHICONE CROSSPOLYMER (SOFT PARTICLE); ORANGE OIL; LIMONENE, (+)-; CAPRYLYL GLYCOL; CYCLOMETHICONE 5; WATER; GLYCERIN; CETYL PEG/PPG-10/1 DIMETHICONE (HLB 4); PHENOXYETHANOL; CARBOMER HOMOPOLYMER, UNSPECIFIED TYPE; ISOMALT; SILICA DIMETHYL SILYLATE; ASCORBIC ACID; SODIUM BENZOATE; HYALURONATE SODIUM; LECITHIN, SOYBEAN; POTASSIUM SORBATE; CYCLOMETHICONE 6; CETEARYL OLIVATE

Drug Facts

Active ingredients

Titanium Dioxide 6.5%

Zinc Oxide 8.7%

Purpose

Sunscreen

Uses

helps prevent sunburn

if used as directed with other sun protection measures (see Directions). decreases the risk of skin cancer and early skin aging caused by the Sun

Warnings

For external use only

Do not use on damaged or broken skin

When using this product keep out of eyes Rinse with water to remove

Stop use and ask a doctor if rash occurs

Keep out of reach of children. If swallowed. get medical help or contact a Poison Control Center right away

DOSAGE AND ADMINISTRATION

Directions • Apply generously 15 minutes before sun exposure • children under 6 months of age: Ask a doctor • reapply at least every 2 hours • use a water resistant sunscreen if swimming or sweating • Sun Protection Measures. Spending time in the sun increase your risk of skin cancer and early skin aging. To decrease this risk regularly use a sunscreen with a Broad Spectrum SPF value of 15 or higher and other sun protection measures inducing: • limit time in the sun, especially from 10 am.-2 p.m. • wear long-sleeved shits, pants, hats and sunglasses

Other information • protect the product in this container from excessive heat and direct sun

Inactive Ingredient:

CYCLOPENTASILOXANE, AQUA/WATER/EAU, C12-15 ALKYL BENZOATE, DIMETHICONE, POLYGLYCERYL-3 POLYDIMETHYLSILOXYETHYL DIMETHICONE, GLYCERIN, ALUMINUM HYDROXIDE, STEARIC ACID, DIMETHICONE/PEG-10/15 CROSSPOLYMER, HELIANTHUS ANNUUS (SUNFLOWER) SEED OIL, SODIUM CHLORIDE, CETYL PEG/PPG-10/1 DIMETHICONE, HEXYL LAURATE, PEG/PPG-18/18 DIMETHICONE, POLYGLYCERYL-4 ISOSTEARATE, PHENOXYETHANOL, DIMETHICONE/POLYGLYCERIN-3 CROSSPOLYMER, DIMETHICONE/VINYL DIMETHICONE CROSSPOLYMER, TRIETHOXYSILYLETHYL POLYDIMETHYLSILOXYETHYL HEXYL DIMETHICONE, CITRUS AURANTIUM DULCIS (ORANGE) PEEL OIL, LIMONENE, CAPRYLYL GLYCOL, CETEARYL OLIVATE, CYCLOHEXASILOXANE, SORBITAN OLIVATE, ETHYLHEXYL PALMITATE, ETHYLHEXYLGLYCERIN, HEXYLENE GLYCOL, CITRUS NOBILIS (MANDARIN ORANGE) PEEL OIL, PEG-8, TOCOPHERYL ACETATE, TOCOPHEROL, ISOMALT, BENZOIC ACID, DIPROPYLENE GLYCOL, PROPYLENE GLYCOL, BUTYLENE GLYCOL, VANILLA PLANIFOLIA FRUIT EXTRACT, SODIUM CITRATE, ASCORBYL PALMITATE, SILICA DIMETHYL SILYLATE, PENTYLENE GLYCOL, ASCORBIC ACID, CITRIC ACID, POLYGONUM AVICULARE EXTRACT, BAROSMA BETULINA LEAF OIL, CAESALPINIA SPINOSA FRUIT POD EXTRACT, CARBOMER, SODIUM LACTATE, SODIUM BENZOATE, POLYSORBATE 20, SODIUM HYALURONATE, LECITHIN, POTASSIUM SORBATE, VITIS VINIFERA (GRAPE) FRUIT CELL EXTRACT, HELIANTHUS ANNUUS (SUNFLOWER) SPROUT EXTRACT, PENTAERYTHRITYL TETRA-DI-T-BUTYL HYDROXYHYDROCINNAMATE, SODIUM FERROCYANIDE, PALMITOYL TRIPEPTIDE-1, PALMITOYL TETRAPEPTIDE-7